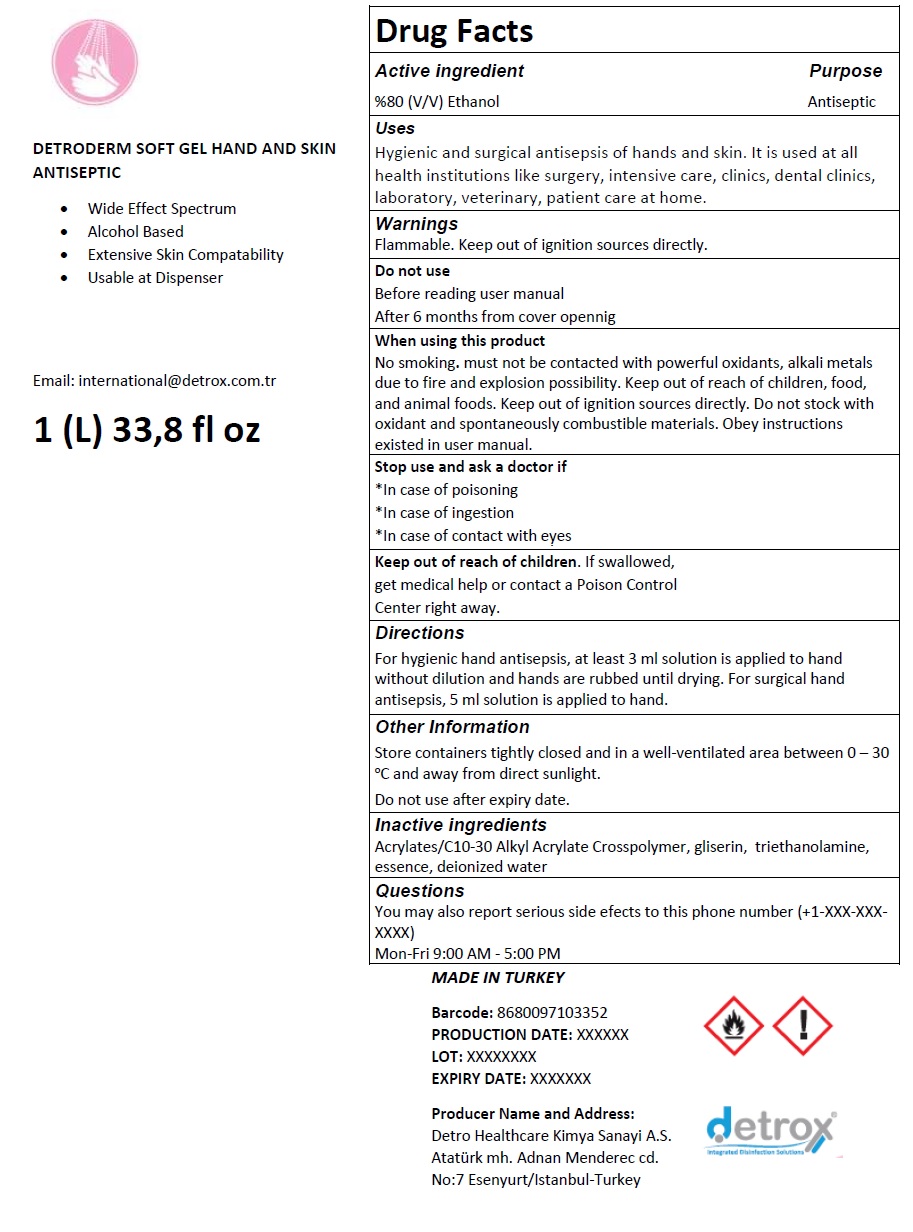 DRUG LABEL: DETRODERM SOFT geL HAND AND SKIN ANTISEPTIC
NDC: 79506-103 | Form: GEL
Manufacturer: DETRO HEALTHCARE KIMYA SANAYI ANONIM SIRKETI
Category: otc | Type: HUMAN OTC DRUG LABEL
Date: 20210420

ACTIVE INGREDIENTS: ALCOHOL 80 mL/100 mL
INACTIVE INGREDIENTS: CARBOMER INTERPOLYMER TYPE A (ALLYL SUCROSE CROSSLINKED); GLYCERIN; TROLAMINE; WATER

DETRODERM SOFT GEL HAND AND SKIN ANTISEPTIC

Active ingredient

%80 (V/V) Ethanol

Purpose

Antiseptic

Uses

Hygienic and surgical antiseptic of hands and skin. It is used at all health institutions like surgery, intensive care, clinics, dental clinics, laboratory, veterinary, patient care at home.

Warnings

Flammable. Keep out of ignition sources directly.

Do not use

Before reading user manual

After 6 months from cover opening

When using this product

No smoking. must not be contacted with powerful oxidants, alkali metals due to fire and explosion possibility. Keep out of reach of children, food and animal foods. Keep out of ignition sources directly. Do not stock with oxidant and spontaneously combustible materials. Obey instructions existed in user manual.

Stop use and ask a doctor if

*In case of poisoning

*In case of ingestion

*In case of contact with eyes

Keep out of reach of children. If swallowed, get medical help or contact a Poison Control Center right away.

Directions

For hygienic hand antiseptic, at least 3 ml solution is applied to hand without dilution and hands are rubbed until drying. For surgical hand antiseptic, 5 ml solution is applied to hand.

Other Information

Store containers tightly closed and in a well-ventilated area between 0-30°C and away from direct sunlight.

Do not use after expiry date.

Inactive ingredients

Acrylates/C10-30 Alkyl Acrylate Crosspolymer, glycerin, triethanolamine, essence, deionized water

Questions

You may also report serious side effects to this phone number (+1-XXX-XXX-XXXX)

Mon-Fri 9:00 AM - 5:00 PM

• Wide Effect Spectrum

• Alcohol Based

• Extensive Skin Compatibility

• Usable at Dispenser

Email: international@detrox.com.tr

MADE IN TURKEY

detrox®

Integrated Disinfection Solutions

Producer Name and Address:

Detro Healthcare Kimya Sanayi A.S.

Ataturk mh. Adnan Menderec cd.

No:7 Esenyurt/Istanbul-Turkey